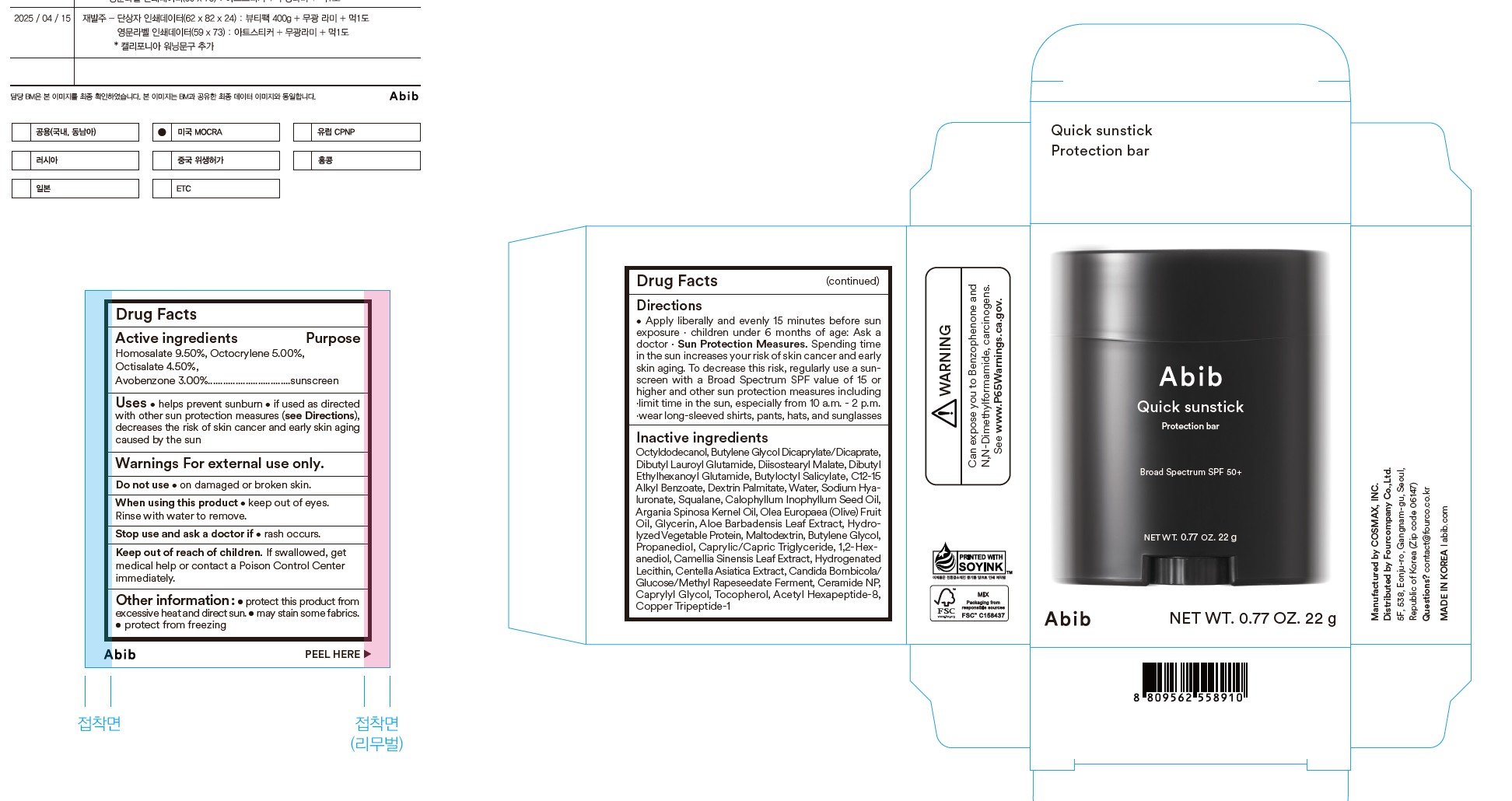 DRUG LABEL: Abib Quick sunstick Protection bar
NDC: 73676-216 | Form: STICK
Manufacturer: FOURCOMPANY CO., LTD.
Category: otc | Type: HUMAN OTC DRUG LABEL
Date: 20251023

ACTIVE INGREDIENTS: AVOBENZONE 3 g/100 g; OCTOCRYLENE 5 g/100 g; HOMOSALATE 9.5 g/100 g; OCTISALATE 4.5 g/100 g
INACTIVE INGREDIENTS: MALTODEXTRIN; BUTYLENE GLYCOL; PROPANEDIOL; PREZATIDE COPPER; BUTYLOCTYL SALICYLATE; ACETYL HEXAPEPTIDE-8; WATER; OLIVE OIL; METHYL RAPESEEDATE; HYALURONATE SODIUM; 1,2-HEXANEDIOL; HYDROGENATED SOYBEAN LECITHIN; BUTYLENE GLYCOL DICAPRYLATE/DICAPRATE; DIISOSTEARYL MALATE; DIBUTYL ETHYLHEXANOYL GLUTAMIDE; GLYCERIN; TOCOPHEROL; DIBUTYL LAUROYL GLUTAMIDE; SQUALANE; MEDIUM-CHAIN TRIGLYCERIDES; ALKYL (C12-15) BENZOATE; CAPRYLYL GLYCOL; DEXTRIN PALMITATE (CORN; 20000 MW); ARGAN OIL; GREEN TEA LEAF; OCTYLDODECANOL; TAMANU OIL; CERAMIDE NP; ALOE VERA LEAF; CENTELLA ASIATICA; HYDROLYZED SENEGALIA MACROSTACHYA SEED PROTEIN (ENZYMATIC; 800 MW); STARMARELLA BOMBICOLA; ANHYDROUS DEXTROSE

Abib
Quick Sunstick Protection Bar

Active ingredients

Homosalate 9.50%, Octocrylene 5.00%, Octisalate 4.50%, Avobenzone 3.00%

Purpose sunscreen

Uses

- help prevent sunburn
- if used as directed with other sun protection measures (see Directions), deacreases the risk of skin cancer and early skin aging caused by the sun

Warnings For external use only.

Do not use on damaged or broken skin

When using this product keep out of eyes. Rinse with water to remove

Stop use and ask a doctor if rash occurs

Keep out of reach of children. If swallowed, get medical help or contact a Poison Control Center immediately.

Other information: protect this product from excessive heat and direct sun. may stain some fabrics. protect from freezing

DOSAGE AND ADMINISTRATION

Directions apply liberally and evenly 15 minutes before sun exposure. reapply: after 80 minutes of swimming or sweating. immediately after towel drying. at least every 2 hours. children under 6 months of age: ask a doctor. Sun protection measures. spending time in the sun increases your risk of skin cancer and early aging. To decrease this risk, regularly use a sunscreen with a Broad Spectrum SPF value of 15 or higher and other sun protection measures including: limit time in the sun, especially from 10 a.m. - 2 p.m., wear long-sleeved shirts, pants, hats, and sunglasses

INACTIVE INGREDIENT

Actives ingredients Octyldodecanol, Butylene Glycol Dicaprylate/Dicaprate, Dibutyl Lauroyl Glutamide, Diisostearyl Malate, Dibutyl Ethylhexanoyl Glutamide, Butyloctyl Salicylate, C12-15 Alkyl Benzoate, Dextrin Palmitate, Water, Sodium Hyaluronate, Squalane, Calophyllum Inophyllum Seed Oil, Argania Spinosa Kegnel Oil, Olea Euro paea (Olive) Fruit Oil, Glycerin, Aloe Barbadensis Leaf Extract, Hydrolyzed Vegetable Protein, Maltodextrin, Butylene Glycol, Propanediol, Caprylic/Capric Trigly ceride, 1,2-Hexanediol, Camellia Sinensis Leaf Extract, Hydrogenated Lecithin, Centella Asiatica Extract, Candida Bombicola/Glucose/Methyl Rapeseedate Fer ment, Ceramide NP, Caprylyl Glycol, Tocopherol, Acetyl Hexapeptide-8, Copper Tripeptide-1

PACKAGE LABEL

Abib
Quick sunstick

Protection bar

Broad Spectrum SPF 50+

NET WT. 0.77 OZ. 22g